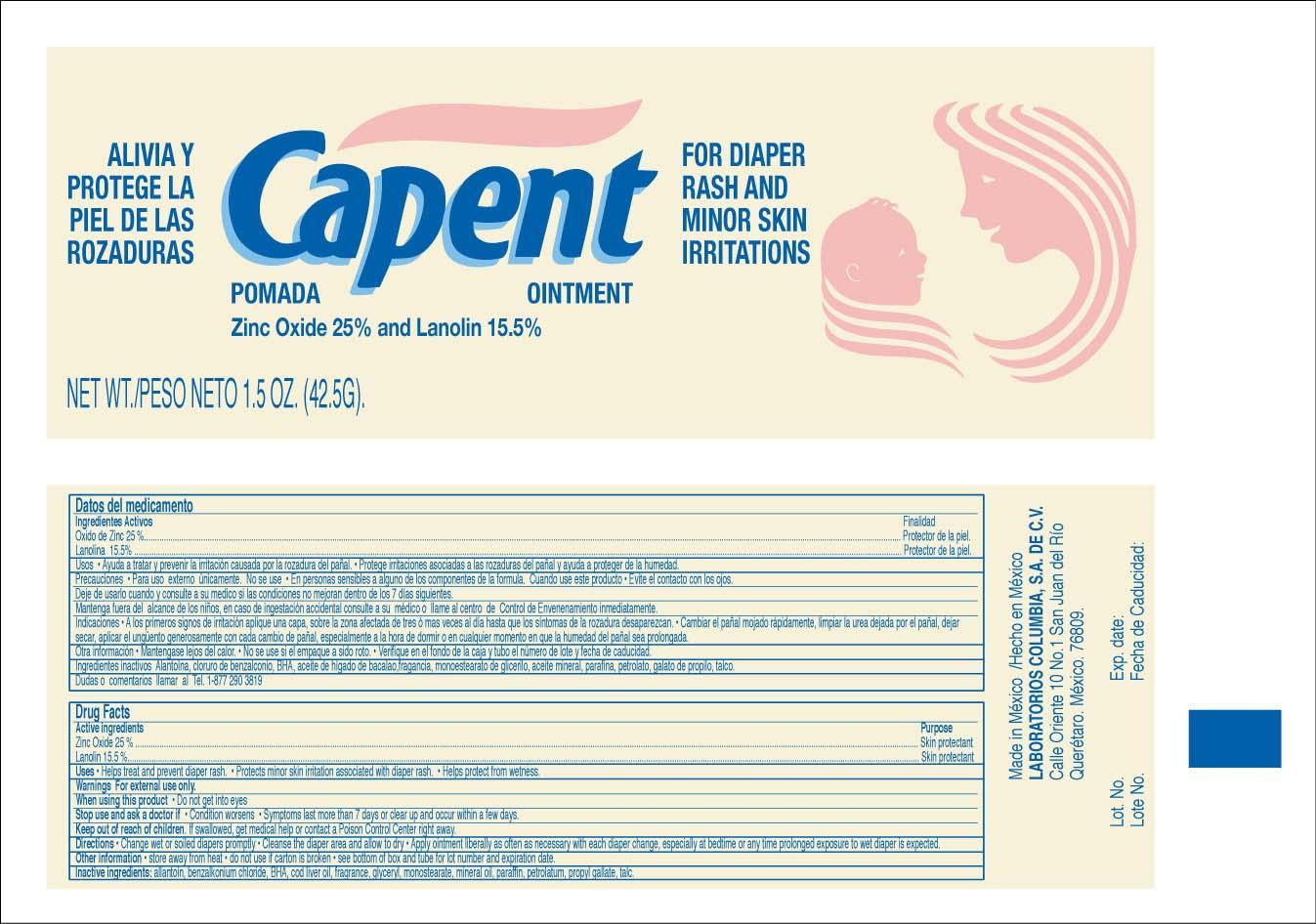 DRUG LABEL: Capent
NDC: 59567-001 | Form: OINTMENT
Manufacturer: Laboratorios Columbia S.A. de C.V.
Category: otc | Type: HUMAN OTC DRUG LABEL
Date: 20130218

ACTIVE INGREDIENTS: ZINC OXIDE 25 g/100 g; LANOLIN 15.5 g/100 g
INACTIVE INGREDIENTS: ALLANTOIN; BENZALKONIUM CHLORIDE; BUTYLATED HYDROXYANISOLE; COD LIVER OIL; GLYCERYL MONOSTEARATE; MINERAL OIL; PARAFFIN; PETROLATUM; PROPYL GALLATE; TALC

Active Ingredients

Zinc Oxide 25%

Lanolin 15.5%

Purpose

Skin protectant

Skin protectant

INDICATIONS AND USAGE

Uses ● Helps treat and prevent diaper rash ●Protects minor skin irritation associated with diaper rash ● Helps protect from wetness

Warnings For external use only

When using this product ● Do not get into eyes

Stop use and ask a doctor if ● Condition worsens ● Symptoms last for more than 7 days or clear up and occur within a few days

Keep out of reach of children. If swallowed get medical help or contact a Poison Control Center right away

DOSAGE AND ADMINISTRATION

Directions ● Change wet or soiled diapers promptly ● Cleanse the diaper area and allow to dry ● Apply ointment liberally as often as necessary with each diaper change, especially at bedtime or any time prolonged exposure to wet diaper is expected

Other information ● store away from heat ● do not use if carton is broken ● see bottom of box and tube for lot number and expiration date

INACTIVE INGREDIENT

Inactive ingredients: allantoin, benzalkonium chloride, BHA, cod liver oil, fragrance, glyceryl monostearate, mineral oil, paraffin, propyl gallate, talc